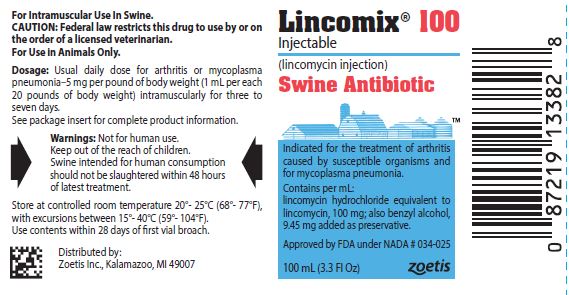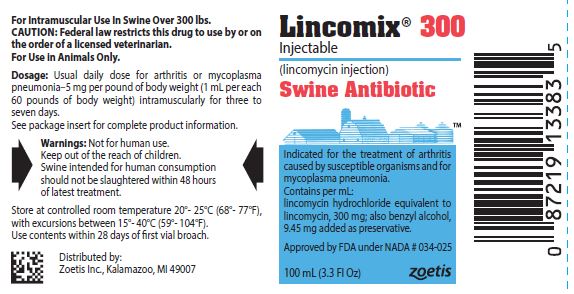 DRUG LABEL: Lincomix
NDC: 54771-0617 | Form: INJECTION
Manufacturer: Zoetis Inc.
Category: animal | Type: PRESCRIPTION ANIMAL DRUG LABEL
Date: 20250924

ACTIVE INGREDIENTS: LINCOMYCIN HYDROCHLORIDE 100 mg/1 mL
INACTIVE INGREDIENTS: BENZYL ALCOHOL 9.45 mg/1 mL

Lincomix®

Lincomix®

brand of lincomycin injection

CAUTION: Federal law restricts this drug to use by or on the order of a licensed veterinarian.

For Intramuscular Use in Swine Only

LINCOMIX Injectable contains lincomycin hydrochloride, an antibiotic produced by Streptomyces lincolnensis var. lincolnensis, which is chemically distinct from all other clinically available antibiotics and is isolated as a white crystalline solid.

INDICATIONS FOR SWINE

LINCOMIX Injectable is indicated for the treatment of infectious forms of arthritis caused by organisms sensitive to its activity. This includes most of the organisms responsible for the various infectious arthritides in swine, such as the staphylococci, streptococci, Erysipelothrix and Mycoplasma spp.
It is also indicated for the treatment of mycoplasma pneumonia.

CONTRAINDICATIONS

As with all drugs, the use of LINCOMIX Injectable is contraindicated in animals previously found to be hypersensitive to the drug.

WARNING

Swine intended for human consumption should not be slaughtered within 48 hours of latest treatment. Not for human use.

CAUTION

If no improvement is noted within 48 hours, consult a veterinarian.

ADVERSE REACTIONS

The intramuscular administration to swine may cause a transient diarrhea or loose stools. Although this effect has rarely been reported, one must be alert to the possibility that it may occur.
Should this occur, it is important that the necessary steps be taken to prevent the effects of dehydration.

DOSAGE AND ADMINISTRATION

For arthritis or mycoplasma pneumonia—5 mg per pound of body weight intramuscularly once daily for three to seven days as needed. When using LINCOMIX Injectable containing 100 mg/mL, 1 mL/20 lb body weight will provide 5 mg/lb. When using LINCOMIX Injectable containing 300 mg/mL, 1 mL/60 lb body weight will provide 5 mg/lb.
For optimal results, initiate treatment as soon as possible.
As with any multi-dose vial, practice aseptic techniques in withdrawing each dose. Adequately clean and disinfect the vial closure prior to entry with a sterile needle and syringe. No vial closure should be entered more than 20 times.

HOW SUPPLIED

LINCOMIX Injectable is available in two concentrations: 300 mg/mL and 100 mg/mL.

300 mg/mL: For use in swine weighing 300 pounds or more. Each mL contains lincomycin hydrochloride equivalent to lincomycin, 300 mg; also Benzyl Alcohol, 9.45 mg added as preservative. Supplied in 100 mL vials.

100 mg/mL: Each mL contains lincomycin hydrochloride equivalent to lincomycin, 100 mg; also Benzyl Alcohol, 9.45 mg added as preservative. Supplied in 100 mL vials.

Store at controlled room temperature 20°-25°C (68°- 77°F), with excursions between 15°- 40°C (59°- 104°F).

Use contents within 28 days of first vial broach.

Approved by FDA under NADA # 034-025
zoetis
Distributed by:
Zoetis Inc.
Kalamazoo, MI 49007
Revised: June 2022
40039342